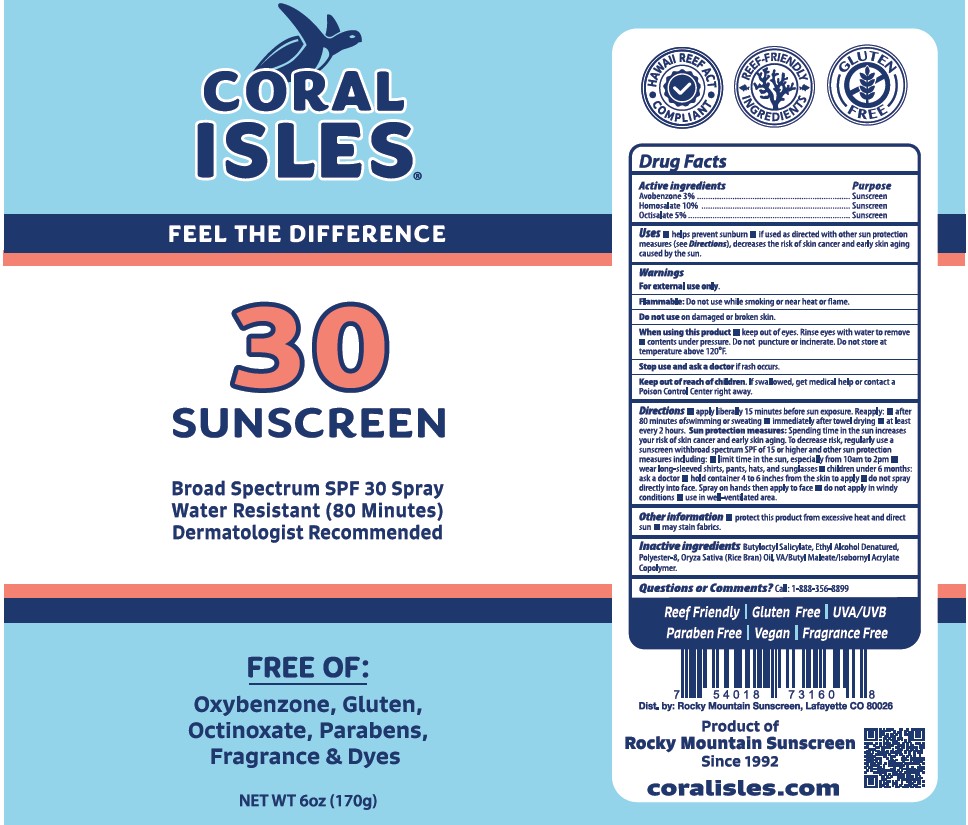 DRUG LABEL: Sunscreen SPF 30
NDC: 49757-012 | Form: SPRAY
Manufacturer: Rocky Mountain
Category: otc | Type: HUMAN OTC DRUG LABEL
Date: 20260114

ACTIVE INGREDIENTS: AVOBENZONE 3 g/100 g; HOMOSALATE 10 g/100 g; OCTISALATE 5 g/100 g
INACTIVE INGREDIENTS: BUTYLOCTYL SALICYLATE; ALCOHOL; POLYESTER-8 (1400 MW, CYANODIPHENYLPROPENOYL CAPPED); ORYZA SATIVA (RICE) SEED OIL

Rocky Mountain SPF 30 Spray (feel the difference)

Uses

■ helps prevent sunburn ■ if used as directed with other sun
protection measures (see Directions), decreases the risk of skin
cancer and early skin aging caused by the sun.

Warnings:

For external use only

Flammable:Do not use white smoking or near heat or flame.

Do not useon damaged or broken skin.
When using this product■ keep out of eyes. Rinse eyes with water
to remove.
Stop use and ask a doctor ifrash occurs.

Keep out of reach of children.

Iswallowed, get medical help or contact a Polson Control Center right away.

Directions

■ apply liberally 15 minutes before sun exposure.
Reapply: ■ after 80 minutes of swimming or sweating ■ Immediately
after towel drying ■ at least every 2 hours. Sun protection
measures:Spending time In the sun Increases your risk of skin
cancer and early skin aging. To decrease risk, regularly use a
sunscreen with broad spectrum SPF of 15 or higher and other sun
protection measures lncludlng: ■ limit time In the sun, especlally
from 10am to 2pm ■ wear long-sleeved shirts, pants, hats, and
sunglasses ■ children under 6 months: ask a doctor ■ do not spray
directly Into face. Spray on hands then apply to face ■ use In
well-ventilated area.

Other information

protect this product from excessive
heat and direct sun ■ may stain fabrics.

Inactive Ingredients

Butyloctyi Sallcylate, Ethyl Alcohol
Denatured, Polyester-8, Oryza Sativa (Rice Bran) Oil, VA/Butyl
Maleate/lsobomyl Acrylate Copolymer.